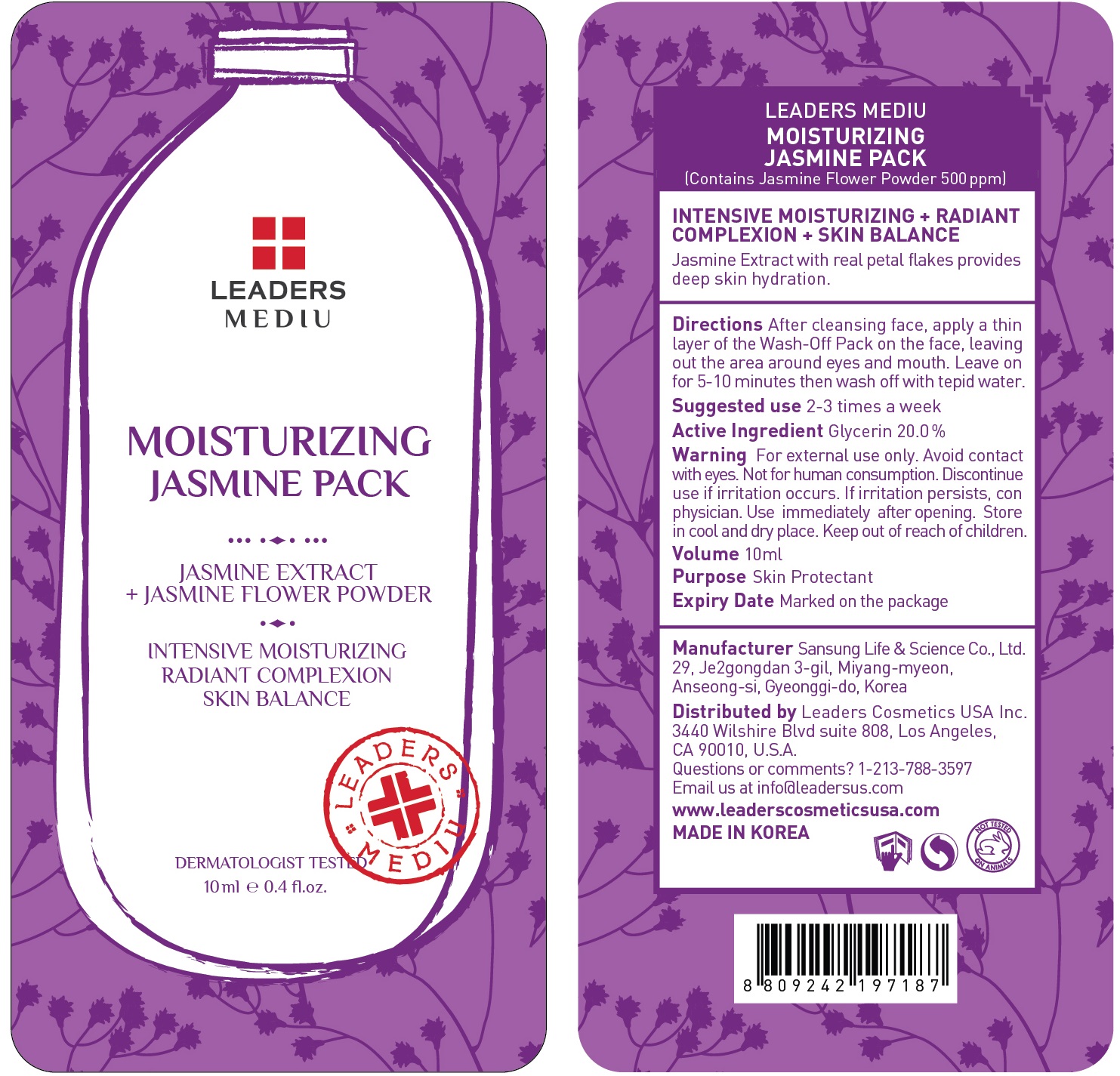 DRUG LABEL: Leaders Mediu Moisturizing Jasmine Pack
NDC: 69424-510 | Form: GEL
Manufacturer: SANSUNG LIFE & SCIENCE CO., LTD.
Category: otc | Type: HUMAN OTC DRUG LABEL
Date: 20160201

ACTIVE INGREDIENTS: Glycerin 2.0 g/10 mL
INACTIVE INGREDIENTS: Water; Butylene Glycol

ACTIVE INGREDIENT

Active Ingredient: Glycerin 20.0%

INACTIVE INGREDIENT

Inactive Ingredients: Water, Butylene Glycol, Dipropylene Glycol, Bis-PEG-18 Methyl Ether Dimethyl Silane, Methyl Gluceth-20, PEG-60 Hydrogenated castor oil, Carbomer, Acrylates/c10-30 Alkyl Acrylate Crosspolymer, Panthenol, Jasminum officinale (Jasmine) flower powder, Rubus idaeus (raspberry) fruit extract, Rosa canina fruit extract, Cornus Officinalis fruit extract, Malpighia emarginata(Acerola) fruit extract, Schizandra chinensis fruit extract, Vaccinium macrocarpon (cranberry) fruit extract, Crataegus oxyacantha fruit extract, Fragaria chiloensis (strawberry) fruit extract, Lycium chinense fruit extract, Rubus coreanus fruit extract, CI 17200, Jasminum officinale (jasmine) extract(300ppm), CI 42090, Triethanolamine, Disodium EDTA, Fragrance, Phenoxyethanol, Chlorphenesin

PURPOSE

Purpose: Skin Protectant

WARNINGS

Warnings: For external use only. Avoid contact with eyes. Not for human consumption. Discontinue use if irritation occurs. If irritation persists, consult a physician.

Use immediately after opening. Store in cool and dry place. Keep out of reach of children.

KEEP OUT OF REACH OF CHILDREN

Directions

Directions: After cleansing face, apply a thin layer of the Wash-Off Pack on the face, leaving out the area around eyes and mouth. Leave on for 5-10 minutes then wash off with tepid water. *Suggested use is 2-3 times a week

Directions

Directions: After cleansing face, apply a thin layer of the Wash-Off Pack on the face, leaving out the area around eyes and mouth. Leave on for 5-10 minutes then wash off with tepid water. *Suggested use is 2-3 times a week